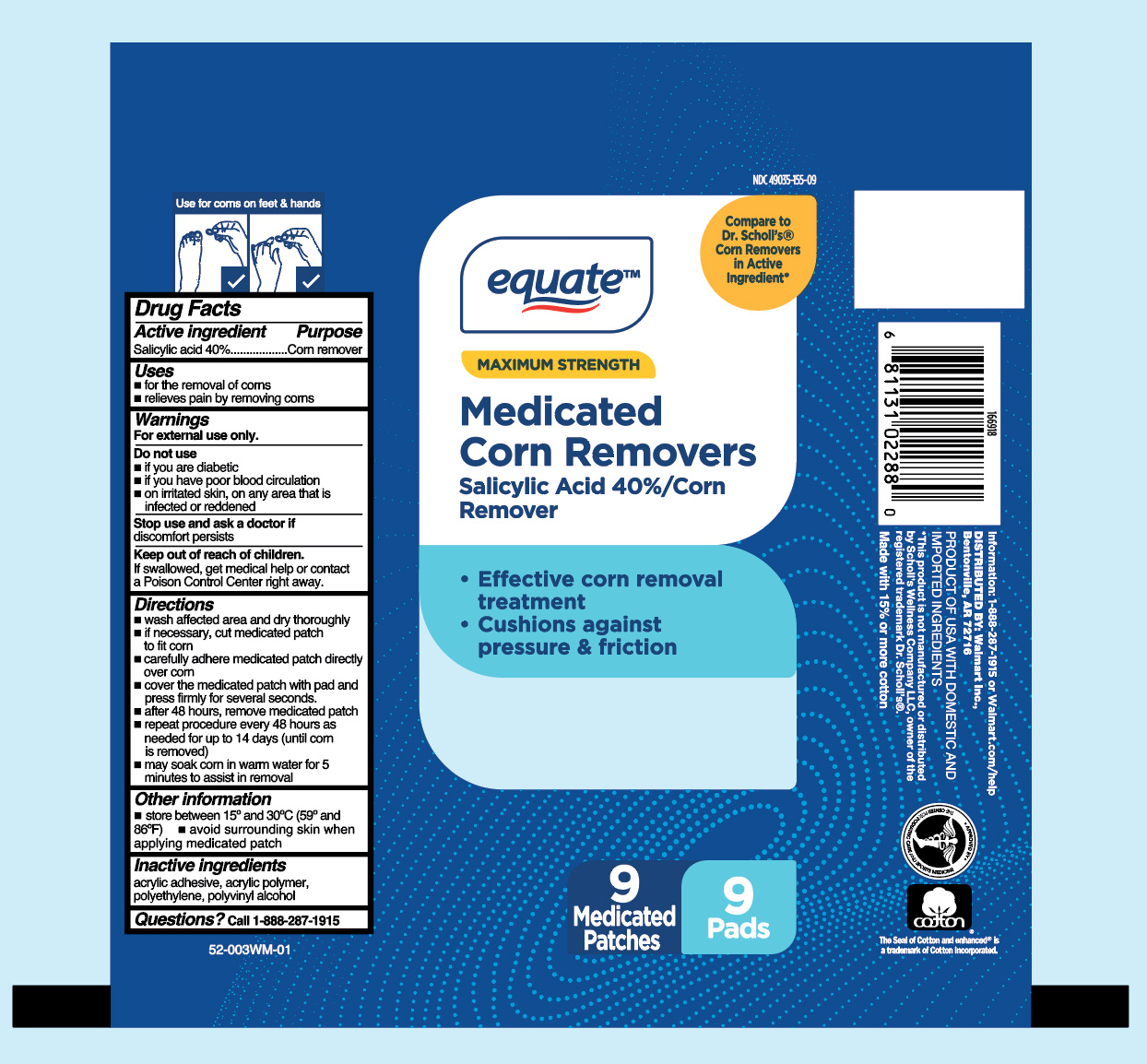 DRUG LABEL: Salicylic acid
NDC: 49035-155 | Form: PATCH
Manufacturer: Wal-Mart Stores Inc
Category: otc | Type: HUMAN OTC DRUG LABEL
Date: 20260121

ACTIVE INGREDIENTS: SALICYLIC ACID 40 mg/9 1
INACTIVE INGREDIENTS: POLYVINYL ALCOHOL, UNSPECIFIED; HIGH DENSITY POLYETHYLENE

Equate Medicated Corn Remover

Active Ingredients

Salicylic acid 40%

Purpose

Corn remover

Uses

- for the removal of corns
- relieves pain by removing corns

Warnings

For external use only.

Do not use

- if you are diabetic
- if you have poor blood circulation
- on irritated skin, on any area that is infected or reddened

Stop use and ask doctor if

discomfort persists

Keep out of reach of children.

If swallowed, get medical help or contact a Poison Control Center right away.

Directions

- wash affected area and dry thoroughly
- if necessary, cut medicated patch to fit corn
- carefully adhere medicated patch directly over corn
- cover the medicated patch with pad and press firmly for several seconds.
- after 48 hours, remove medicated patch
- repeat procedure every 48 hours as needed for up to 14 days (until corn is removed)
- may soak corn in warm water for 5 minutes to assist in removal

Other Information

- store between 15° and 30°C (59° and 86°F)
- avoid surrounding skin when applying medicated patch

Inactive Ingredients

acrylic adhesive, acrylic polymer, polyethylene, polyvinyl alcohol

Questions?

1-888-287-1915

Principal Display Panel

equate

MAXIMUM STRENGTH

Medicated

Corn Removers

Salicylic Acid 40% / Corn

Remover

- Effective corn removal

treatment

- Cushions against

pressure & friction

9 Medicated Patches 9 Pads